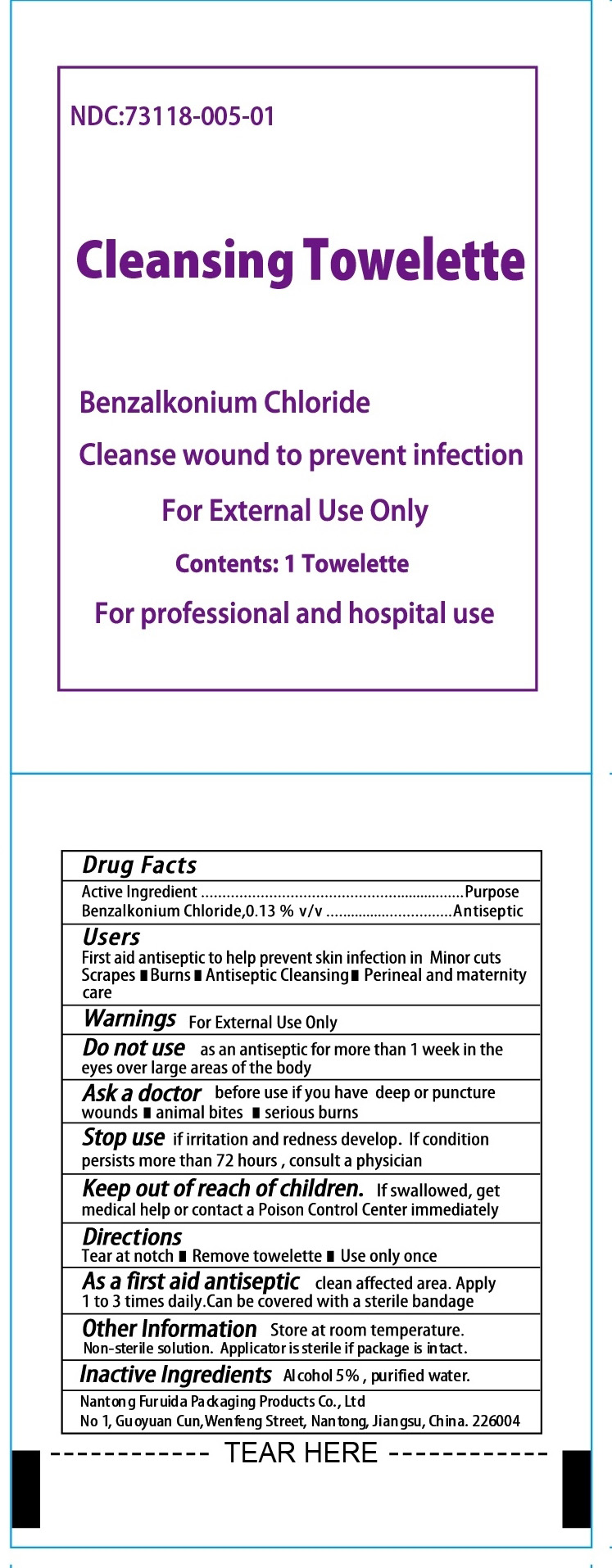 DRUG LABEL: Cleansing Towelette
NDC: 73118-005 | Form: SWAB
Manufacturer: Nantong Furuida Packaging Products Co., Ltd.
Category: otc | Type: HUMAN OTC DRUG LABEL
Date: 20210524

ACTIVE INGREDIENTS: BENZALKONIUM CHLORIDE 0.13 mg/1 1
INACTIVE INGREDIENTS: WATER; ALCOHOL

73118-005

Active Ingredients

Benzalkonium Chloride 0.13%

Purpose

Antiseptic

Use

Cleasing of face,hands and body without soap and water.Air dryies in seconds.

Non-sterile solution

Applicator is sterile if package is intact.

Warnings

For external use only
Flammable,keep away for fire or flame

Do not use:

* In large quantities
* over large areas of the body
* in eyes
* over raw or blistered areas

Stop use and ask a doctor if conditions worsen or persist for more than 7 days or clear up and occur again within a few days.

Keep out of reach of children.if swallowed get medical help or contact Poison control Center right away.

Directions

Adults and Children 2 year and older; Apply to cleaned affected area not more than 3 times daily.
Children under 2 years of age ; Consult a doctor

Inactive Ingredient

5% v/v alcohol,Purified Water